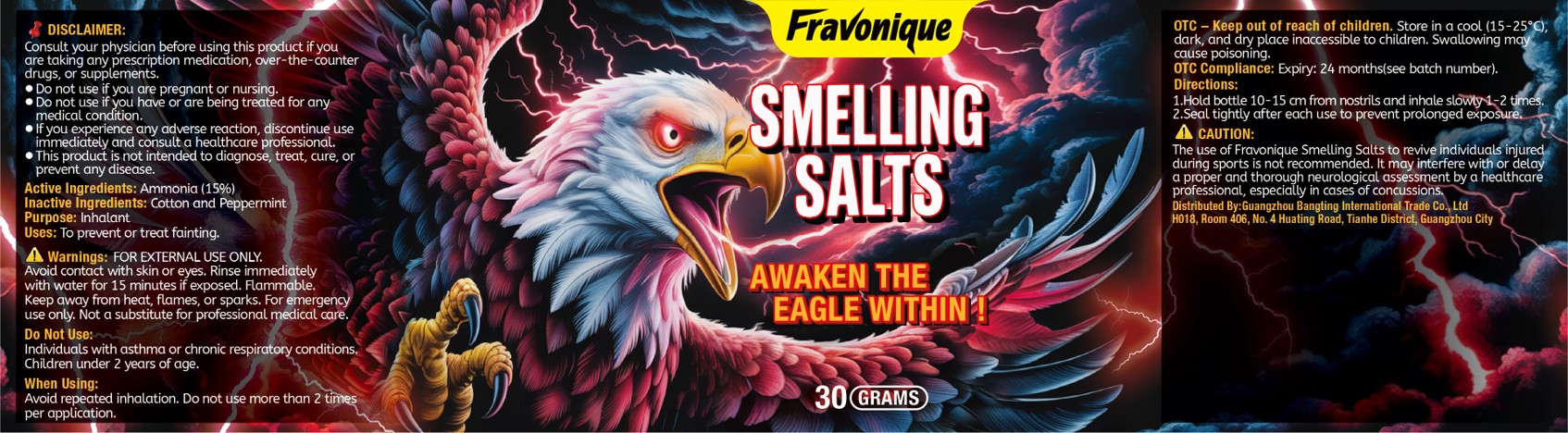 DRUG LABEL: Smelling Salt
NDC: 87055-001 | Form: INHALANT
Manufacturer: Guangzhou Bangting International Trade Co., Ltd
Category: otc | Type: HUMAN OTC DRUG LABEL
Date: 20250821

ACTIVE INGREDIENTS: AMMONIUM CARBONATE 15 g/100 g
INACTIVE INGREDIENTS: COTTON; PEPPERMINT

87055-001 Smelling Salt

ACTIVE INGREDIENT

Ammonium Carbonate 15%

PURPOSE

Inhalant

INDICATIONS AND USAGE

Uses: To prevent or treat fainting.

WARNINGS

FOR EXTERNAL USE ONLY.
Avoid contact with skin or eyes. Rinse immediately
with water for 15 minutes if exposed, Flammable.
Keep away from heat, flames, or sparks. For emergency
use only, Not a substitute for professional medical care.

DO NOT USE

Individuals with asthma or chronic respiratory conditions.
Children under 2 years of age.
Do not use if you are pregnant or nursing.
Do not use if you have or are being treated for anymedical condition.

WHEN USING

Avoid repeated inhalation. Do not use more than 2 times
per application.

KEEP OUT OF REACH OF CHILDREN

OTC-Keep out of reach of children. Store in a cool (15-25°C) dark, and dry place inaccessible to children. Swallowing may cause poisoning.

STOP USE

If you experience any adverse reaction, discontinue useimmediately and consult a healthcare professional.

DOSAGE AND ADMINISTRATION

1.Hold bottle 10-15 cm from nostrils and inhale slowty 1-2 times.
2.Seal tightly after each use to prevent prolonged exposure.

INACTIVE INGREDIENT

Cotton
Peppermint Flavour